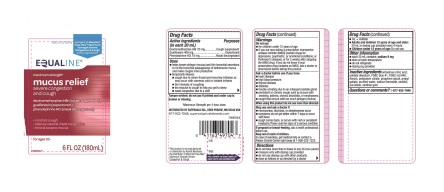 DRUG LABEL: maximum strength mucus relief severe congestion and cough
NDC: 41163-738 | Form: LIQUID
Manufacturer: SuperValu Inc.,
Category: otc | Type: HUMAN OTC DRUG LABEL
Date: 20170901

ACTIVE INGREDIENTS: dextromethorphan hydrobromide 20 mg/20 mL; guaifenesin 400 mg/20 mL; phenylephrine hydrochloride 10 mg/20 mL
INACTIVE INGREDIENTS: anhydrous citric acid; edetate disodium; FD&C Blue NO. 1; FD&C Red NO. 40; POTASSIUM CITRATE; propylene glycol; propyl gallate; water; sodium benzoate; sorbitol; sucralose; xanthan gum

Equaline®maximum strength‡ mucus relief severe congestion and cough 6 FL OZ (180 mL)

Drug Facts

ACTIVE INGREDIENT

PURPOSE

Active ingredients (in each 20 mL) | Purposes
Dextromethorphan HBr 20 mg | Cough suppressant
Guaifenesin 400 mg | Expectorant
Phenylephrine HCl 10 mg | Nasal decongestant

Uses

- helps loosen phlegm (mucus) and thin bronchial secretions to rid the bronchial passageways of bothersome mucus and make coughs more productive
- temporarily relieves:
  - cough due to minor throat and bronchial irritation as may occur with the common cold or inhaled irritants
  - the intensity of coughing
  - the impulse to cough to help you get to sleep
  - nasal congestion due to a cold

Warnings

Do not use

- for children under 12 years of age
- if you are now taking a prescription monoamine oxidase inhibitor (MAOI) (certain drugs for depression, psychiatric, or emotional conditions, or Parkinson's disease), or for 2 weeks after stopping the MAOI drug. If you do not know if your prescription drug contains an MAOI, ask a doctor or pharmacist before taking this product.

Ask a doctor before use if you have

- heart disease
- high blood pressure
- thyroid disease
- diabetes
- trouble urinating due to an enlarged prostate gland
- persistent or chronic cough such as occurs with smoking, asthma, chronic bronchitis or emphysema
- cough that occurs with too much phlegm (mucus)

When using this product

do not use more than directed

Stop use and ask a doctor if

- nervousness, dizziness or sleeplessness occur
- symptoms do not get better within 7 days or occur with fever
- cough comes back, or occurs with rash or persistent headache. These could be signs of a serious condition.

PREGNANCY OR BREAST FEEDING

If pregnant or breast-feeding, ask a health professional before use.

Keep out of reach of children. In case of overdose, get medical help or contact a Poison Control Center right away 1-800-222-1222

Directions

- do not take more than 6 doses in any 24-hour period
- measure only with dosing cup provided
- do not use dosing cup with other products
- dose as follows or as directed by a doctor
- mL = milliliter
- Adults and children 12 years of age and older: 20 mL in dosing cup provided every 4 hours.
- Children under 12 years of age: Do not use.

Other information

- each 20 mL contains: sodium 8 mg
- store at room temperature
- do not refrigerate
- dosing cup provided

Inactive ingredients

anhydrous citric acid, edetate disodium, FD&C Blue #1, FD&C Red #40, flavors, potassium citrate, propylene glycol, propyl gallate, purified water, sodium benzoate, sorbitol, sucralose, xanthan gum

Questions or comments?

1-866-932-7948

PRINCIPAL DISPLAY PANEL

EQUALINE®

NDC 41163-738-06

Compare to Mucinex® Fast- Max™ Maximum strength Severe Congestion & Cough active ingredients*

maximum strength‡

severe congestion and cough

dextromethorphan HBr (cough suppressant)
guaifenesin (expectorant)
phenylephrine HCl (nasal decongestant)

- controls cough
- relieves nasal and chest congestion
- thins and loosens mucus

6 FL OZ (180 mL)

for ages 12+

Tamper evident: do not use if printed seal under cap is broken or missing.

‡Maximum Strength per 4 hour dose.

DISTRIBUTED BY SUPERVALU INC., EDEN PRAIRIE, MN 55344 USA

877-932-7948, supervaluprivatebrands.com

‡Maximum Strength per 4 hour dose.

*This product is not manufactured or distributed by Reckitt Benckiser, the distributor of Mucinex ®

Fast -Max® Maximum Strength Severe Congestion & Cough.